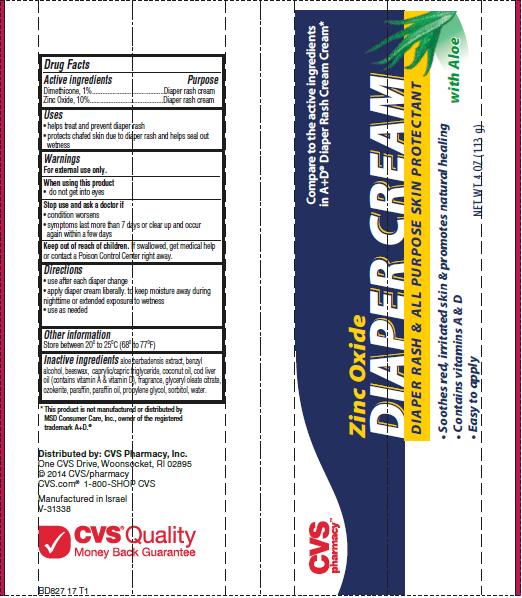 DRUG LABEL: Diaper Rash
NDC: 59779-827 | Form: CREAM
Manufacturer: CVS Pharmacy
Category: otc | Type: HUMAN OTC DRUG LABEL
Date: 20140521

ACTIVE INGREDIENTS: DIMETHICONE 1 g/100 g; ZINC OXIDE 10 g/100 g
INACTIVE INGREDIENTS: ALOE VERA LEAF; BENZYL ALCOHOL; ROYAL JELLY; MEDIUM-CHAIN TRIGLYCERIDES; COCONUT OIL; COD LIVER OIL; GLYCERYL OLEATE; CERESIN; PARAFFIN; MINERAL OIL; PROPYLENE GLYCOL; SORBITOL; WATER

CVS pharmacy™ Zinc Oxide Diaper Cream

Active ingredient

Dimethicone, 1%
Zinc Oxide, 10%

Purpose

Diaper rash cream

Uses

- helps treat and prevent diaper rash
- protects chafed skin due to diaper rash and helps seal out wetness

Warnings

For external use only.

When using this product

- do not get into eyes

Stop use and ask a doctor if

- condition worsens
- symptoms last more than 7 days or clear up and occur again within a few days

Keep out of reach of children.

If swallowed, get medical help or contact a Poison Control Center right away.

Directions

- use after each diaper change
- apply diaper cream liberally to keep moisture away during nighttime or extended exposure to wetness
- use as needed

Other Information

Store between 20° to 25°C (68° to 77°F)

Inactive Ingredients

aloe barbadensis extract, benzyl alcohol, beeswax, caprylic/capric triglyceride, coconut oil, cod liver oil (contains vitamin A & vitamin D), fragrance, glyceryl oleate citrate, ozokerite, parafﬁn, parafﬁn oil, propylene glycol, sorbitol, water.

Package/Label Principal Display Panel - Carton Label

CVS pharmacy™

Zinc Oxide
Diaper Cream
Diaper Rash & All Purpose Skin Protectant

- Soothes red, irritated skin & promotes natural healing
- Contains vitamins A & D
- Easy to apply

Compare to the active ingredients in A+D® Diaper Rash Cream*

*This product is not manufactured or distributed by MSD Consumer Care, Inc., owner of the registered trademark A+D®.

Carton Label